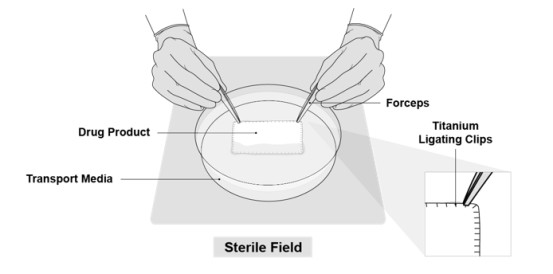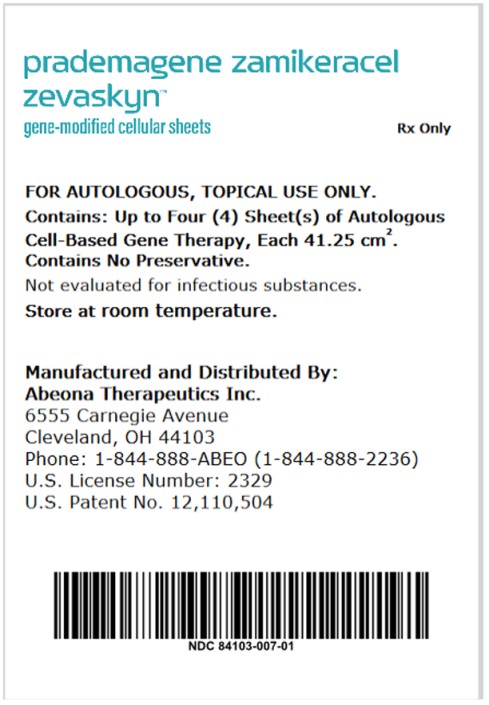 DRUG LABEL: ZEVASKYN
NDC: 84103-007 | Form: CELLULAR SHEET
Manufacturer: Abeona Therapeutics Inc.
Category: prescription | Type: HUMAN PRESCRIPTION DRUG LABEL
Date: 20250413

ACTIVE INGREDIENTS: PRADEMAGENE ZAMIKERACEL 40 cm2/1 1
INACTIVE INGREDIENTS: GLYCINE; ALANINE; ARGININE HYDROCHLORIDE; ASPARAGINE MONOHYDRATE; ASPARTIC ACID; CYSTEINE; GLUTAMIC ACID; GLUTAMINE; HISTIDINE MONOHYDROCHLORIDE; ISOLEUCINE; LEUCINE; LYSINE HYDROCHLORIDE; METHIONINE; PHENYLALANINE; PROLINE; SERINE; THREONINE; TRYPTOPHAN; TYROSINE; VALINE; CHOLINE CHLORIDE; PANTOTHENIC ACID; FOLIC ACID; INOSITOL; NIACINAMIDE; PYRIDOXAL HYDROCHLORIDE; RIBOFLAVIN; THIAMINE HYDROCHLORIDE; CYANOCOBALAMIN; BIOTIN; AMMONIUM METAVANADATE; AMMONIUM MOLYBDATE; CALCIUM CHLORIDE; CUPRIC SULFATE; FERRIC SULFATE; MAGNESIUM CHLORIDE; MANGANESE SULFATE; NICKEL CHLORIDE; POTASSIUM CHLORIDE; SODIUM ACETATE; SODIUM BICARBONATE; SODIUM CHLORIDE; SODIUM METASILICATE; SODIUM PHOSPHATE, DIBASIC, ANHYDROUS; SODIUM SELENITE; STANNOUS CHLORIDE; ZINC SULFATE HEPTAHYDRATE; ADENINE HYDROCHLORIDE; ANHYDROUS DEXTROSE; ARLIPOIC ACID; 2-AMINOETHANOL; HYDROXYETHYLPIPERAZINE ETHANE SULFONIC ACID; PHOSPHORYLCOLAMINE; PHENOLSULFONPHTHALEIN; PUTRESCINE DIHYDROCHLORIDE; SODIUM PYRUVATE; THYMIDINE; BOS TAURUS PITUITARY GLAND; MECASERMIN; BOVINE TRANSFERRIN (IRON FREE); HYDROCORTISONE; HUMAN EPIDERMAL GROWTH FACTOR; FERROUS SULFATE; HUMAN TRANSFERRIN HOLO; HYDROCHLORIC ACID; NICKEL SULFATE HEPTAHYDRATE; PYRIDOXINE HYDROCHLORIDE; INSULIN HUMAN; SODIUM SULFATE ANHYDROUS; LIOTHYRONINE

HIGHLIGHTS OF PRESCRIBING INFORMATION

These highlights do not include all the information needed to use ZEVASKYN™ safely and effectively. See full prescribing information for ZEVASKYN.
ZEVASKYN (prademagene zamikeracel), gene-modified cellular sheets, for topical use
Initial U.S. Approval: 2025

1 INDICATIONS AND USAGE

ZEVASKYN is an autologous cell sheet-based gene therapy indicated for the treatment of wounds in adult and pediatric patients with recessive dystrophic epidermolysis bullosa (RDEB). (1)

2 DOSAGE AND ADMINISTRATION

For autologous topical application on wounds only

- The recommended dose of ZEVASKYN is based on the surface area of the wound(s). One sheet of ZEVASKYN covers an area of 41.25 cm^2. (2.1)
- Up to twelve ZEVASKYN sheets may be manufactured from the patient biopsies and supplied for potential use. (2.1)
- Verify the patient’s identity prior to ZEVASKYN application. (2.2)
- See full prescribing information for ZEVASKYN preparation, and administration instructions. (2.2, 2.3)

3 DOSAGE FORMS AND STRENGTHS

ZEVASKYN is supplied as a single-dose of up to twelve cellular sheets each measuring 41.25 cm^2 (5.5 cm x 7.5 cm) and consisting of patient's own, viable, gene-modified cells that contain functional copies of the COL7A1 gene, which express collagen 7 (C7) protein. (3)

4 CONTRAINDICATIONS

None.

5 WARNINGS AND PRECAUTIONS

- Hypersensitivity reactions to vancomycin, amikacin, or product excipients may occur with ZEVASKYN application. (5.1)
- Retroviral vector (RVV)-mediated insertional oncogenesis may potentially occur after treatment with ZEVASKYN. (5.2)
- Transmission of Infectious Agents may occur because ZEVASKYN is manufactured using human- and bovine-derived reagents. (5.3)

6 ADVERSE REACTIONS

The most common adverse reactions (incidence ≥5%) were procedural pain and pruritus. (6)

To report SUSPECTED ADVERSE REACTIONS, contact Abeona Therapeutics Inc at 1-844-888-2236 or the FDA at 1-800-FDA-1088 or www.fda.gov/medwatch.

FULL PRESCRIBING INFORMATION

1 INDICATIONS AND USAGE

ZEVASKYN is indicated for the treatment of wounds in adult and pediatric patients with recessive dystrophic epidermolysis bullosa (RDEB).

2 DOSAGE AND ADMINISTRATION

2.1 Recommended Dose

For autologous topical application on wounds only.

- The recommended dose of ZEVASKYN is based on the surface area of the wound(s).
- One sheet of ZEVASKYN covers an area of 41.25 cm^2.
- Up to twelve ZEVASKYN sheets may be manufactured from the patient biopsies and supplied for potential use.

2.2 Receipt and Preparation

Receipt of ZEVASKYN

- ZEVASKYN is shipped directly to the qualified treatment center sealed in transport packaging.
- If the patient is expected to be ready for same-day application, transport the packaging to the operating room. Hold at room temperature (15-25°C) until preparation to maintain cell viability.
- If the patient is not expected to be ready for same-day application, store the packaging containing ZEVASKYN in a secure onsite location at room temperature (15-25°C) until preparation to maintain cell viability.

Preparation

- ZEVASKYN is to be prepared by the manufacturer in an appropriate healthcare setting for surgical application by a qualified healthcare provider.
- Manufacturer will conduct Quality Control (QC) testing to release the product immediately prior to surgery in the operating room.
- Verify patient’s identity during preparation.
- Hold ZEVASKYN at room temperature (15-25°C) until application.
- Apply all selected sheets in a single surgical session.

2.3 Administration

Below is the list of standard surgical supplies needed for ZEVASKYN administration and not provided by the manufacturer:

- scalpel
- scissors
- forceps
- resorbable sutures
- non-adhesive dressings
- topical antibiotic ointment

1. Verify patient’s identity prior to ZEVASKYN application. Do not apply ZEVASKYN if the information on the patient-specific label(s) does not match the intended patient.

2. Prepare wound by debridement under general or other appropriate anesthesia to accommodate ZEVASKYN sheet(s).

3. Before surgical application, pick up ZEVASKYN sheet with forceps by grasping the titanium ligating clips (Figure 1). Handle ZEVASKYN sheets only with forceps and only by the titanium ligating clips.

Figure 1. ZEVASKYN sheets removed with forceps for application

4. Do not trim ZEVASKYN sheets.

5. Apply unaltered ZEVASKYN sheets onto the wound bed only (nylon suture on the ZEVASKYN sheet facing away from wound) by affixing via resorbable sutures. Do not suture ZEVASKYN onto healthy intact skin. Do not overlap ZEVASKYN sheets on wounds.

6. Apply all selected sheets in a single surgical session.

7. Cover area of application of ZEVASKYN sheets with non-adhesive dressings and topical antibiotic ointment.

After ZEVASKYN application

8. Instruct patient to leave the treated area undisturbed for 5-10 days at the discretion of the physician based on individual needs for immobilization of treated areas and post-surgical recovery.

9. Instruct patient to keep dressings dry and not submerge the treated area in water until the gauze of the ZEVASKYN product falls off the treatment site. Gauze backing should fall off within 2-3 weeks of ZEVASKYN surgical application.

3 DOSAGE FORMS AND STRENGTHS

ZEVASKYN is supplied as single-dose cellular sheets each measuring 41.25 cm^2 (5.5 cm x 7.5 cm) and consisting of patient's own viable, gene-modified cells that contain functional copies of the COL7A1 gene, which express collagen 7 (C7) protein.

Up to twelve (12) C7-expressing cellular sheets are supplied for each surgical session (supplied as up to 3 containers containing up to 4 sheets).

4 CONTRAINDICATIONS

None.

5 WARNINGS AND PRECAUTIONS

5.1 Hypersensitivity Reactions

Severe hypersensitivity reactions to vancomycin, amikacin, or product excipients may occur with ZEVASKYN application. Monitor for signs and symptoms of hypersensitivity reactions such as itching, swelling, hives, difficulty breathing, runny nose, watery eyes, nausea, and in severe cases, anaphylaxis and treat according to standard clinical practice.

5.2 Retroviral Vector (RVV)-Mediated Insertional Oncogenesis

RVV-mediated insertional oncogenesis may potentially occur after treatment with ZEVASKYN [see Nonclinical Toxicology (13)]. Monitor patients lifelong after treatment with ZEVASKYN for the development of malignancies. In the event that a malignancy occurs, contact Abeona Therapeutics Inc. at 1-844-888-2236 to obtain instructions on collecting patient samples for testing.

5.3 Transmission of Infectious Agents

Transmission of infectious disease or agents may occur with ZEVASKYN administration because it is manufactured using human and bovine-derived reagents, which are tested for human and animal viruses, bacteria, fungi, and mycoplasma before use. These measures do not eliminate the risk of transmitting these or other infectious diseases or agents.

6 ADVERSE REACTIONS

6.1 Clinical Trials Experience

Because clinical trials are conducted under widely varying conditions, adverse reaction rates observed in the clinical trials of a product cannot be directly compared to the rates in the clinical trials of another product and may not reflect the rates observed in practice.

The safety data described in this section reflects exposure of 11 patients to ZEVASKYN in the VIITAL study [see Clinical Studies (14)].

The median number of sheets patients received was 6 (range 3-6), and the total exposure time was 6 months following ZEVASKYN application.

The most common adverse reactions occurring in ≥5% of patients were procedural pain (n=3; 27%) and pruritus (n=1; 9%).

8 USE IN SPECIFIC POPULATIONS

8.1 Pregnancy

Risk Summary

There are no available data with ZEVASKYN use in pregnant women. No animal reproductive and developmental toxicity studies have been conducted with ZEVASKYN.

The estimated background risk of major birth defects and miscarriage for the indicated population is unknown. In the U.S. general population, the estimated background risk of major birth defects and miscarriage in clinically recognized pregnancies is 2-4% and 15-20%, respectively.

Clinical Considerations

Women of childbearing potential should be advised to use an effective method of contraception to prevent pregnancy at the time of treatment with ZEVASKYN.

8.2 Lactation

Risk Summary

There is no information regarding the presence of ZEVASKYN in human milk, its effect on the breastfed infant, or its effects on milk production. Animal lactation studies have not been conducted with ZEVASKYN.

The developmental and health benefits of breastfeeding should be considered along with the mother’s clinical need for ZEVASKYN and any potential adverse effects on the breast-fed infant from ZEVASKYN or from the underlying maternal condition.

8.3 Females and Males of Reproductive Potential

No studies were performed to evaluate the effect of ZEVASKYN on fertility.

8.4 Pediatric Use

The safety and effectiveness of ZEVASKYN have been established in pediatric patients. The use of ZEVASKYN in pediatric patients was supported by evidence from one clinical study which included two pediatric patients aged 6 years and 16 years [see Adverse Reactions (6) and Clinical Studies (14)].

8.5 Geriatric Use

The safety and effectiveness of ZEVASKYN have not been studied in geriatric patients ≥ 65 years of age.

11 DESCRIPTION

ZEVASKYN is composed of autologous cells isolated from skin punch biopsies of patients with mutations in the collagen type VII alpha 1 chain (COL 7A1) gene and which have been transduced ex vivo with a replication-incompetent retroviral vector (RVV) containing the full-length COL7A1 gene. The resulting gene-modified cell sheets express functional collagen VII (C7) protein. ZEVASKYN is manufactured using human- and animal-derived reagents.

ZEVASKYN is provided as cellular sheets of 41.25 cm^2 (5.5 cm x 7.5 cm) secured to sterile petrolatum gauze using sterile ligation titanium clips for surgical application. The cellular sheets consist of autologous, viable, gene-modified cells. Up to twelve (12) sheets may be manufactured from the patient biopsies and supplied for potential use.

Each ZEVASKYN sheet is packaged in a clamshell and sealed transport pouch containing sterile transport media. The transport media includes reagents derived from human and animal materials, including bovine pituitary extract, bovine transferrin, and human transferrin. The sheet also has a nylon suture, which functions as a visual indicator of the sheet’s topography. Neither ZEVASKYN sheets nor its excipients contain preservatives.

12 CLINICAL PHARMACOLOGY

12.1 Mechanism of Action

In patients with recessive dystrophic epidermolysis bullosa (RDEB), both copies of the COL7A1 gene are mutated, resulting in the absence or low levels of biologically active C7 protein which form anchoring fibrils (AFs). The lack of AFs disrupts the connection between the epidermis and the dermis and causes skin fragility and other signs and symptoms of RDEB. ZEVASKYN consists of a patient's own cells that have been gene-modified through RVV transduction to express the COL7A1 gene to produce the C7 protein. These cells are formed into cellular sheets for topical application onto wounds.

12.2 Pharmacodynamics

In a single-arm clinical study (n=7), C7 was assessed by both immunofluorescence and the presence of AFs at Months 3, 6, and 12. The NC2 domain of C7 was assessed using the LH24 antibody, and the presence of AFs was assessed by immunoelectron microscopy. The NC2 domain of C7 and AFs were detected in 6 patients at 3 months and in 5 patients at 6 months. One year after treatment with ZEVASKYN, 3 patients were positive for NC2 or AFs. At Year 2, 2 out of 3 patients with biopsies were positive for NC2 or AFs (1 patient was positive for both AFs and NC2; the second patient was positive only for NC2, as an additional biopsy for AF assessment was not obtained).

12.3 Pharmacokinetics

No clinical studies have been conducted to evaluate the pharmacokinetics of ZEVASKYN.

12.6 Immunogenicity

The observed incidence of anti-drug antibodies is highly dependent on the sensitivity and specificity of the assay. Differences in assay methods preclude meaningful comparisons of the incidence of anti-drug antibodies in the studies described below with the incidence of anti-drug antibodies in studies with other products.

In a single-arm clinical study, anti-C7 antibodies against Type VII collagen were assessed in 7 patients at baseline, 1, 3, and 6 months and then annually for 5 years at physician’s discretion after treatment with ZEVASKYN. Out of 7 patients, circulating anti-C7 antibodies were detected in 2 patients which resolved at 1 year follow-up. Tissue-bound anti-C7 antibodies were detected in 4 patients which resolved in 3 patients at 1 year follow-up. In 1 patient with positive baseline anti-C7 antibodies, localized immunoreactants were observed at treated sites for up to 2 years after treatment.

In the VIITAL study, anti-C7 antibodies were assessed at baseline and at physician’s discretion at Months 3 and 6. Eight patients were biopsied at either Month 3 or 6, and none of those patients tested positive for C7 immune complexes [see Clinical Studies (14)].

Because of the small sample size, there is limited data to determine the effect of anti-C7 antibodies on the pharmacodynamics, safety, and/or effectiveness of ZEVASKYN.

13 NONCLINICAL TOXICOLOGY

13.1 Carcinogenesis, Mutagenesis, Impairment of Fertility

No carcinogenicity studies have been conducted with ZEVASKYN. Integration site analysis in RDEB keratinocytes transduced with LZRSE-Col7A1 showed a low level of integration distributed throughout the host genome with no predilection to specific integration sites, including in genes associated with malignant transformation in humans. No studies have been conducted to evaluate the effects of ZEVASKYN on fertility.

14 CLINICAL STUDIES

The efficacy of ZEVASKYN was evaluated in a multi-center, randomized, intrapatient-controlled study (VIITAL; NCT04227106). The study compared the application of ZEVASKYN to the standard of care treatment in patients with wounds associated with recessive dystrophic epidermolysis bullosa (RDEB). For enrollment, the patients were required to have at least one pair of matched, large (at least one wound ≥20 cm^2 for treatment and at least one wound ≥20 cm^2 for control) and chronic wounds (open for ≥6 months) associated with RDEB. Patients with current or history of squamous cell carcinoma (SCC) at the treatment site were excluded. Matched wound pairs were randomized in a 1:1 ratio to receive either ZEVASKYN (up to 6 sheets) or control treatment (standard of care wound dressings).

A total of 86 wounds in 11 patients were enrolled and treated with ZEVASKYN or standard of care in the study. The demographic characteristics of the population were as follows: the mean age was 23 years (range 6 to 40 years) including 2 pediatric patients (aged 6 and 16 years), 7 patients (64%) were female, 10 patients (91%) were White, 1 patient (9%) was of unknown race, and 2 patients (18%) were Hispanic or Latino. The wounds assessed in the study at baseline had been open for a median of 5 years (range 0.5-21 years).

The co-primary efficacy outcome measures were 1) proportion of randomized wound pairs with at least 50% healing at Month 6 with confirmation of wound healing two weeks later as assessed using baseline digital photography by the Investigator, and 2) pain reduction as assessed by the mean differences in patient-reported pain scores using the Wong-Baker FACES scale between randomized wound pairs at Month 6.^1 Secondary outcome measures were proportion of randomized wound pairs with complete wound healing defined as reepithelialization with no drainage or erosion and presence of only minor crusting from baseline at Month 3 and at Month 6 with confirmation of wound healing two weeks later.

The efficacy results are summarized in Table 2.

Table 2: Efficacy results for VIITAL Study (N=86 wounds)
Efficacy endpoint | ZEVASKYN (N=43 wounds) | Control (N=43 wounds) | P value
Proportion of randomized wound pairs healed ≥50% from baseline at Month 6a n (%) | 35 (81%) | 7 (16%) | <0.0001
Mean pain reduction from baseline at Month 6b Mean (SD) | -3.07 (3.19) | -0.90 (2.73) | 0.0002
Proportion of randomized wound pairs completely healed from baseline at Month 3 n (%) | 6 (14%) | 0 (0%) | 0.0316
Proportion of randomized wound pairs completely healed from baseline at Month 6a n (%) | 7 (16%) | 0 (0%) | 0.0160

N=total number of observations; SD=Standard deviation; %=percentage

Complete wound healing is defined as re-epithelialization with no drainage or erosion and presence of only minor crusting.

a The proportion of wounds achieving success criteria at Month 6 must have been confirmed at least 2 weeks later.

b One wound was excluded from the control group due to missing baseline value.

15 REFERENCES

1. Wong-Baker FACES Foundation. Wong-Baker FACES Pain Rating Scale. Retrieved 24 July 2023 with permission from http://www.WongBakerFACES.org. Originally published in Whaley & Wong’s Nursing Care of Infants and Children. Elsevier Inc. 2022.

16 HOW SUPPLIED/STORAGE AND HANDLING

16.1 How Supplied

ZEVASKYN sheets of 41.25 cm² (5.5 cm × 7.5 cm) affixed on a rectangular gauze and placed in a clear, thermoformed protective case (“clamshell”) containing sterile transport media sealed in packaging consisting of 4 levels of protection.

Up to four ZEVASKYN sheets are provided in a single transport container, with up to three containers per manufactured lot, for a total of up to twelve sheets. All available sheets per manufactured lot are supplied under NDC 84103-007-01.

- Confirm patient identity on the drug product container upon receipt.
- Each sheet is supplied ready for use and is intended for application on the patient from whom the biopsy was derived for manufacturing the ZEVASKYN sheet.

Due to ZEVASKYN’s autologous nature, in case of a manufacturing failure, a second manufacturing of ZEVASKYN may be attempted and would require a repeat biopsy.

16.2 Storage and Handling

Store and transport ZEVASKYN at room temperature (15-25°C). ZEVASKYN is stable for 84 hours at room temperature and must be used within 84 hours. Dispose of any compromised or mishandled product.

Dispose of unused ZEVASKYN as surgical biohazardous waste in accordance with local requirements.

Dispose of materials that have come into contact with ZEVASKYN as surgical biohazardous waste in accordance with local requirements.

17 PATIENT COUNSELING INFORMATION

Discuss the following with patients and/or caregivers.

- Hypersensitivity Reactions: Inform patients and/or caregivers that hypersensitivity reactions may occur with ZEVASKYN application. Advise patients and/or caregivers to seek immediate medical evaluation if any signs and symptoms of hypersensitivity reaction occur, such as itching, swelling, hives, difficulty breathing, runny nose, watery eyes, nausea, and in severe cases, anaphylaxis [see Warnings and Precautions (5.1)].
- Insertional Oncogenesis: Inform patients and/or caregivers about the possible risk of insertional oncogenesis and development of malignancies with ZEVASKYN application [see Warnings and Precautions (5.2)].
- Transmission of Infectious Agents: Inform patients and/or caregivers about the possible risk of transmission of infectious agents with ZEVASKYN application [see Warnings and Precautions (5.3)].
- Post-application care:
  - Expect pain and itching at the treatment site during the healing process. Contact the treating physician if experiencing fever, increased drainage, worsening pain and/or swelling or any other adverse effect at or around the treatment site [see Adverse Reactions (6)].
  - Do not disturb the surgical dressing covering the ZEVASKYN epidermal sheet for 5-10 days. Leave the post-procedure surgical dressing in place unless instructed otherwise by the treating physician [see Dosage and Administration (2.3)].
  - Keep the dressing(s) dry. Do not submerge treated sites in water until the gauze of the ZEVASKYN falls off the treatment site. Gauze backing should fall off within 2-3 weeks of ZEVASKYN surgical application [see Dosage and Administration (2.3)].

- Manufacturing Failure: Inform patients and/or caregivers that manufacturing failure may occur with autologous products. In case of a manufacturing failure, a second manufacturing of ZEVASKYN could be attempted with a new biopsy [see How Supplied (16.1)].

Manufactured and Distributed by:
Abeona Therapeutics Inc.
6555 Carnegie Avenue
Cleveland, OH 44103
Ph.: 1-844-888-2236
U.S. License Number 2329
U.S. Patent No. 12,110,504

© 2025 Abeona Therapeutics Inc. All rights reserved.

PRINCIPAL DISPLAY PANEL

prademagene zamikeracel
zevaskyn
gene-modified cellular sheets
Rx Only